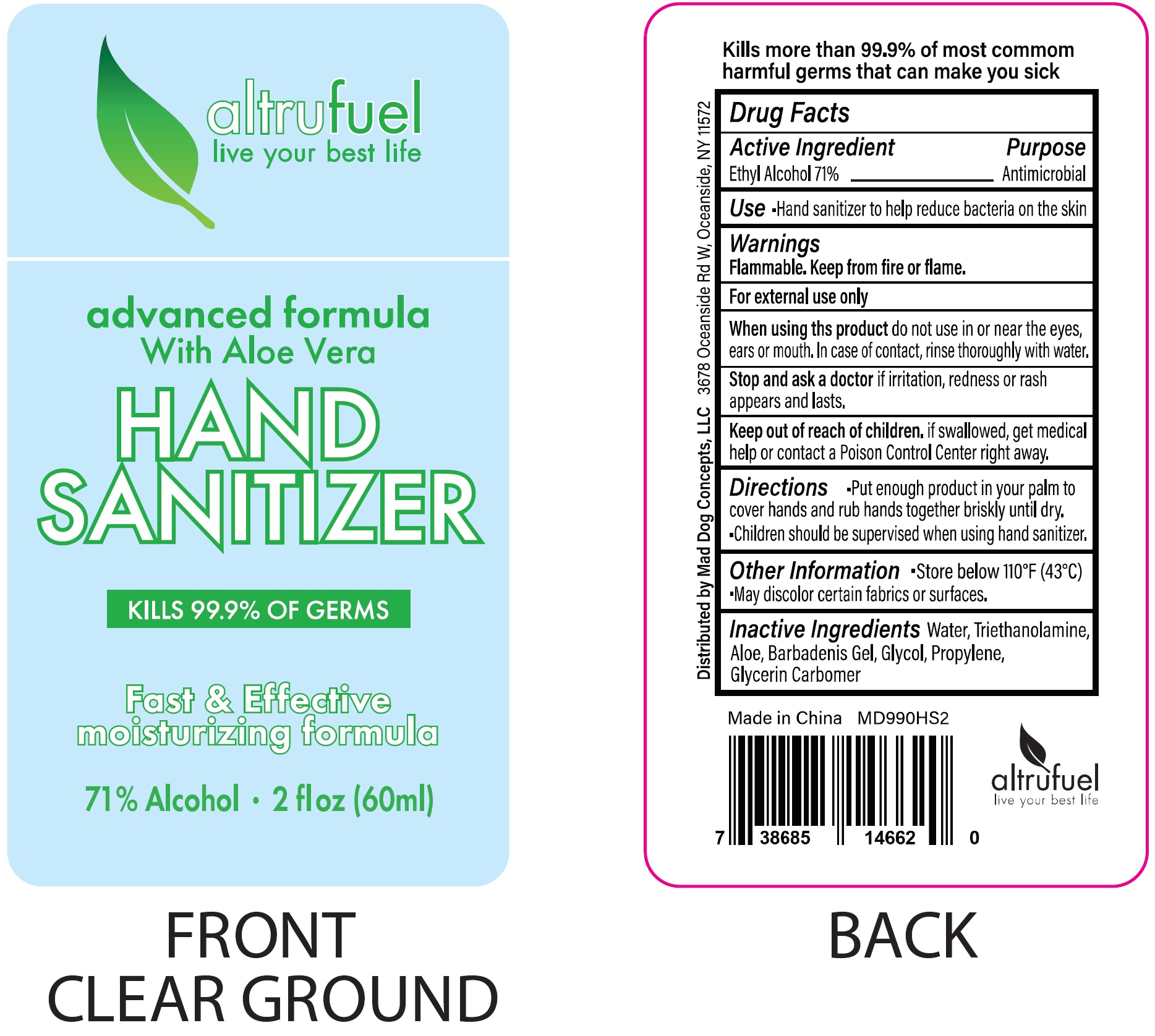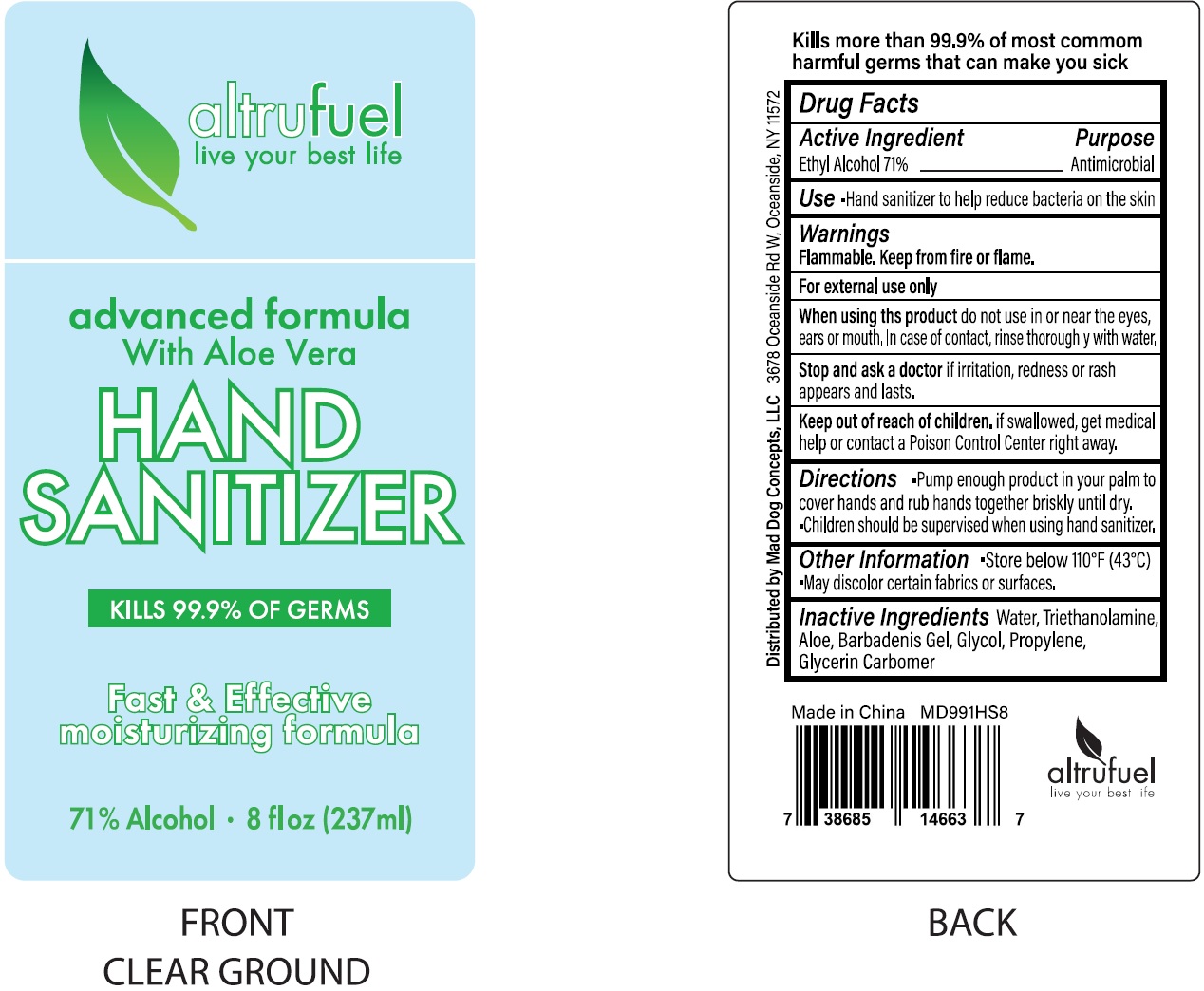 DRUG LABEL: Altrufuel Hand Sanitizer
NDC: 75421-000 | Form: LIQUID
Manufacturer: Mad Dog Concepts, LLC
Category: otc | Type: HUMAN OTC DRUG LABEL
Date: 20200819

ACTIVE INGREDIENTS: ALCOHOL 0.71 mL/1 mL
INACTIVE INGREDIENTS: WATER; TROLAMINE; ALOE; ETHYLENE GLYCOL; PROPYLENE; GLYCERIN; CARBOMER HOMOPOLYMER, UNSPECIFIED TYPE

Altrufuel Hand Sanitizer

Active Ingredient

Ethyl Alcohol 71%

Purpose

Antimicrobial

Use

Hand sanitizer to help reduce bacteria on the skin

Warnings

Flammable. Keep from fire or flame.

For external use only

When using this proudct

Do not use in or near the eyes, ears or mouth. In case of contact, rinse thoroughly with water.

Stop use and ask a doctor

if irritation, redness or rash appears and lasts.

Keep out of reach of children.

if swallowed, get medical help or contact a Poison Control Center right away.

Directions

Put enough product in your palm to cover hands and rub hands together briskly until dry.

Children should be supervised when using hand sanitizer.

Other Information

- Store below 110°F (43°C)
- May discolor certain fabrics or surfaces.

Inactive Ingredients

Water, Triethanolamine, Aloe, Barbadensis Gel, Glycol, Propylene, Glycerin, Carbomer